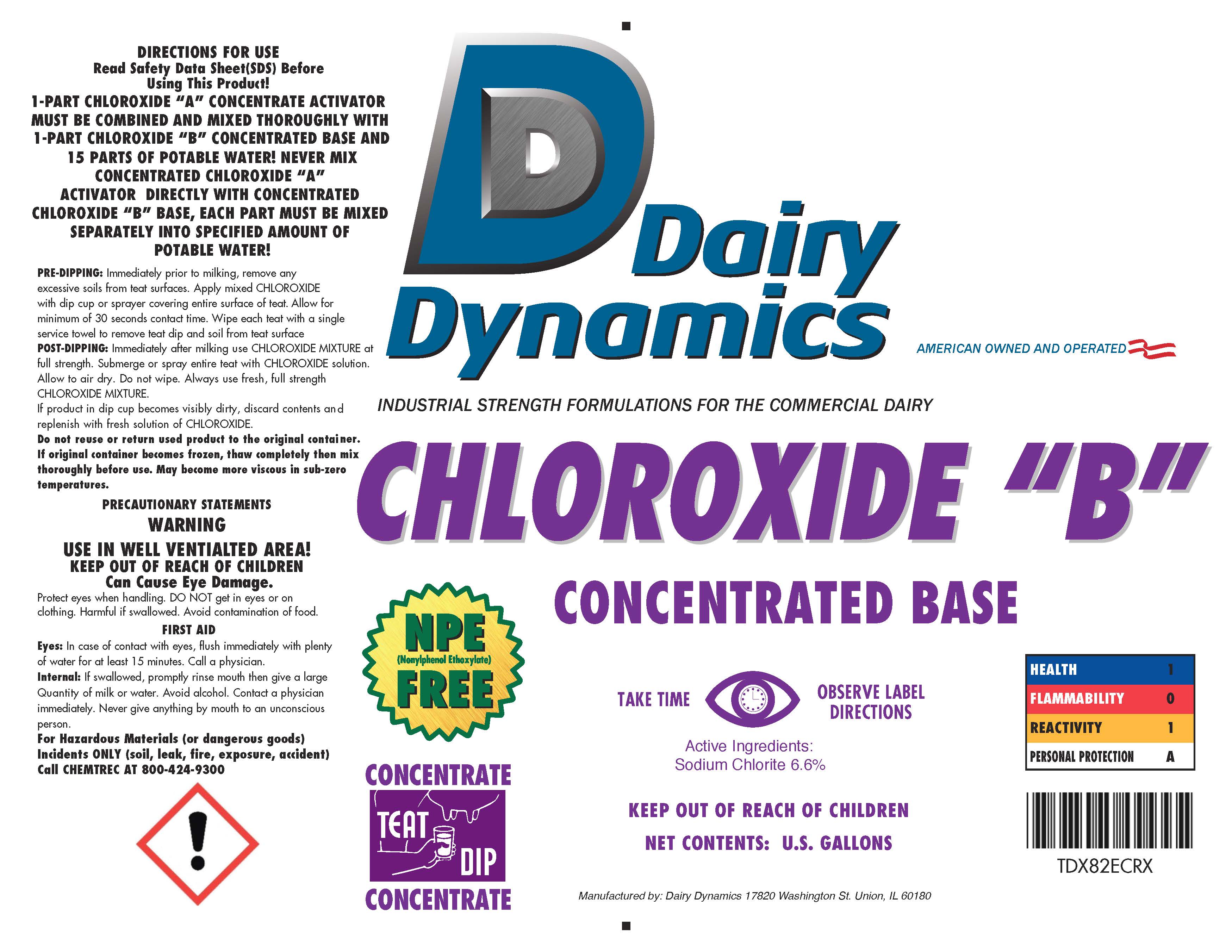 DRUG LABEL: Chloroxide B
NDC: 67351-982 | Form: CONCENTRATE
Manufacturer: Dairy Dynamics L.L.C.
Category: animal | Type: OTC ANIMAL DRUG LABEL
Date: 20190509

ACTIVE INGREDIENTS: SODIUM CHLORITE 66.0 g/1 L
INACTIVE INGREDIENTS: WATER; TRISODIUM NITRILOTRIACETATE

CHLOROXIDE "B"
Concentrated Activator

DIRECTIONS FOR USE

Read Safety Data Sheet (SDS) Before Using This Product!

1-PART CHLORIOXIDE "A' CONCENTRATE ACTIVATOR MUST BE COMBINED AND MIXED THOROUGHLY WITH 1-PART CHLOROXIDE "B" CONCENTRATED BASE AND 15 PARTS OF POTABLE WATER! NEVER MIX CONCENTRATED CHLOROXIDE "A" ACTIVATOR DIRECTLY WITH CONCENTRATED CHLOROXIDE "B" BASE, EACH PART MUST BE MIXED SEPARATELY INTO SPECIFIED AMOUNT OF POTABLE WATER!

PRE-DIPPING: Immediately propr to milking, remove any excessive soils from teat surfaces. Apply mixed CHLOROXIDE with dip cup or sprayer covering entire surface of teat. Allow for minimum of 30 seconds contact time. Wipe each teat with a single service towel to remove teat dip and soil from teat surface.

POST-DIPPING: Immediately after milking use CHLOROXIDE MIXTURE at full strength. Submerge or spray entire teat with CHLOROXIDE solution. Allow to air dry. Do not wipe. Always use fresh, full strength CHLOROXIDE MIXTURE.

If product in dip cup becomes visibly dirty, discard contents and replenish with fresh solution of CHLOROXIDE.

WARNINGS

Do not reuse or return used product to the original container. If original container becomes frozen, thaw completely then mix thoroughly before use. May become more viscous in sub-zero temperatures.

PRECAUTIONS

PRECAUTIONARY STATEMENTS

WARNING

USE IN WELL VENTILATED AREA!

KEEP OUT OF REACH OF CHILDREN

PRECAUTIONS

CAN CAUSE EYE DAMAGE.

Protect eyes when handling. DO NOT get in eyes or on clothing. Harmful if swallowed. Avoid contamination of food.

FIRST AID

Eyes: In case of contact with eyes, flush immediately with plenty of water for at least 15 minutes. Call a physician.

Internal: If swallowed, promptly rinse mouth then give a large Quantify of milk or water. Avoid alcohol. Contact a physician immediately. Never give anything by mouth to an unconscious person.

For Hazardous Materials (or dangerous goods) Incidents ONLY (soil, leak, fire, exposure, accident)

Call CHEMTREC AT 1-800-424-9300

!

NPE

(Nonylphenol Ethoxylate)

FREE

CONCENTRATE

TEAT DIP

CONCENTRATE

Active Ingredients:

Sodium Chlorite 6.6%

TAKE TIME OBSERVE LABEL DIRECTIONS

HEALTH 1

FLAMMABILITY 0

REACTIVITY 1

PERSONAL PROTECTION A

NET CONTENTS: U.S. GALLONS

Manufactured by:

Dairy Dynamics

17820 Washington St.

Union, IL 60180